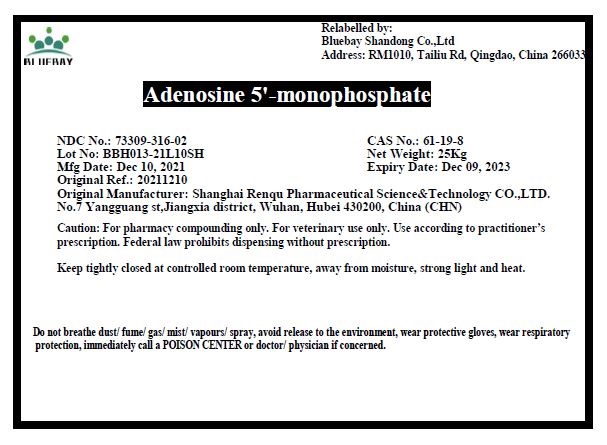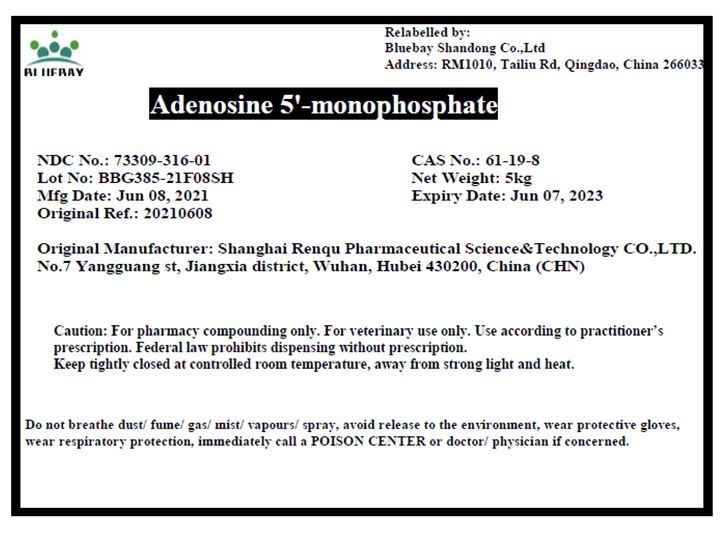 DRUG LABEL: Adenosine 5monophosphate
NDC: 73309-316 | Form: POWDER
Manufacturer: BLUEBAY SHANDONG CO.,LTD
Category: other | Type: BULK INGREDIENT
Date: 20220114

ACTIVE INGREDIENTS: ADENOSINE PHOSPHATE 1 kg/1 kg

Adenosine 5 monophosphate